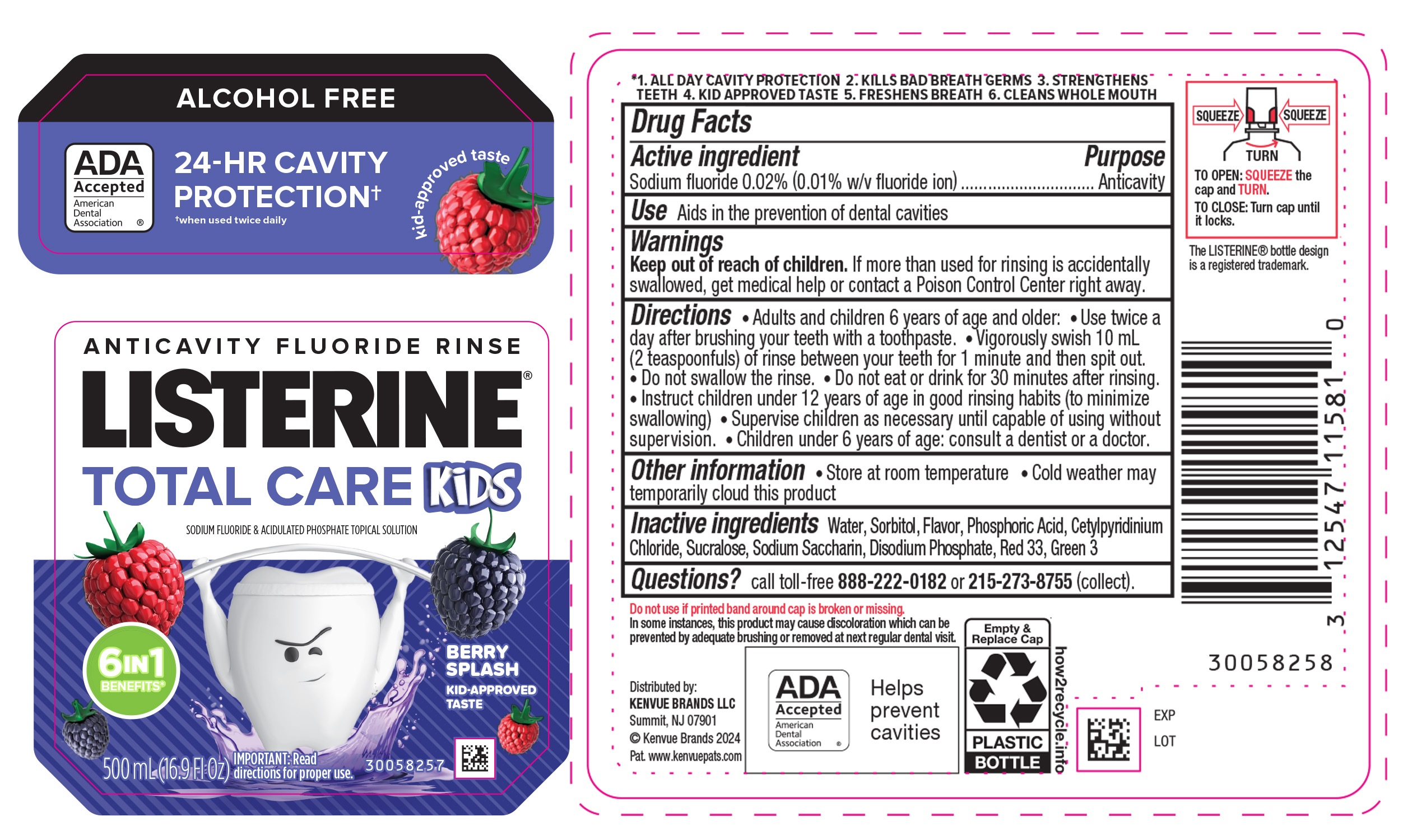 DRUG LABEL: Listerine Total Care Kids Anticavity Fluoride Rinse - Berry Splash
NDC: 69968-0904 | Form: MOUTHWASH
Manufacturer: Kenvue Brands LLC
Category: otc | Type: HUMAN OTC DRUG LABEL
Date: 20251210

ACTIVE INGREDIENTS: SODIUM FLUORIDE 0.1 mg/1 mL
INACTIVE INGREDIENTS: SORBITOL; WATER; PHOSPHORIC ACID; CETYLPYRIDINIUM CHLORIDE; SUCRALOSE; SACCHARIN SODIUM; SODIUM PHOSPHATE, DIBASIC, ANHYDROUS; D&C RED NO. 33; FD&C GREEN NO. 3

Listerine Total Care Kids Anticavity Fluoride Rinse - Berry Splash

Drug Facts

Active ingredient

Sodium fluoride 0.02% (0.01% w/v fluoride ion)

Purpose

Anticavity

Use

Aids in the prevention of dental cavities

Warnings

Keep out of reach of children. If more than used for rinsing is accidentally swallowed, get medical help or contact a Poison Control Center right away.

Directions

- Adults and children 6 years of age and older:
- Use twice a day after brushing your teeth with a toothpaste.
- Vigorously swish 10 mL (2 teaspoonfuls) of rinse between your teeth for 1 minute and then spit out.
- Do not swallow the rinse.
- Do not eat or drink for 30 minutes after rinsing.
- Instruct children under 12 years of age in good rinsing habits (to minimize swallowing)
- Supervise children as necessary until capable of using without supervision.
- Children under 6 years of age: consult a dentist or a doctor.

Other information

- Store at room temperature
- Cold weather may temporarily cloud this product

Inactive ingredients

Water, Sorbitol, Flavor, Phosphoric Acid, Cetylpyridinium Chloride, Sucralose, Sodium Saccharin, Disodium Phosphate, Red 33, Green 3

Questions?

call toll-free 888-222-0182 or 215-273-8755 (collect).

Distributed by:
KENVUE BRANDS LLC

Summit, NJ 07901

PRINCIPAL DISPLAY PANEL - 500 mL Bottle Label

ALCOHOL FREE

ADA
Accepted

American

Dental

Association ®

24-HR CAVITY

PROTECTION†

†when used twice daily

kid-approved taste

ANTICAVITY FLUORIDE RINSE

LISTERINE®

TOTAL CARE KiDS

SODIUM FLUORIDE & ACIDULATED PHOSPAHTE TOPICAL SOLUTION

6IN1

BENEFITS*

BERRY

SPLASH

KID-APPROVED

TASTE

500mL(16.9Fl Oz)

IMPORTANT: Read

directions for proper use.